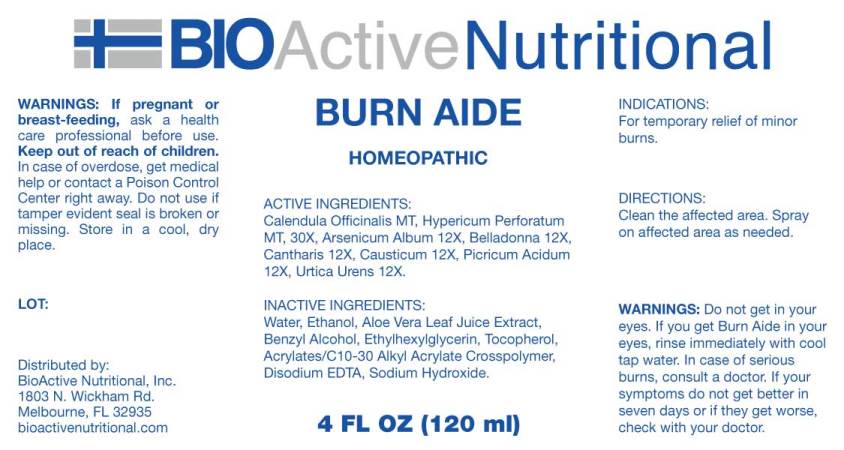 DRUG LABEL: Burn Aide
NDC: 43857-0472 | Form: SPRAY
Manufacturer: BioActive Nutritional, Inc.
Category: homeopathic | Type: HUMAN OTC DRUG LABEL
Date: 20241022

ACTIVE INGREDIENTS: CALENDULA OFFICINALIS FLOWERING TOP 1 [hp_X]/1 mL; HYPERICUM PERFORATUM WHOLE 1 [hp_X]/1 mL; ARSENIC TRIOXIDE 12 [hp_X]/1 mL; ATROPA BELLADONNA 12 [hp_X]/1 mL; LYTTA VESICATORIA 12 [hp_X]/1 mL; CAUSTICUM 12 [hp_X]/1 mL; PICRIC ACID 12 [hp_X]/1 mL; URTICA URENS WHOLE 12 [hp_X]/1 mL
INACTIVE INGREDIENTS: WATER; ALOE VERA LEAF; BENZYL ALCOHOL; ETHYLHEXYLGLYCERIN; TOCOPHEROL; CARBOMER INTERPOLYMER TYPE A (ALLYL SUCROSE CROSSLINKED); EDETATE DISODIUM ANHYDROUS; SODIUM HYDROXIDE; ALCOHOL

DRUG FACTS:

ACTIVE INGREDIENTS:

Calendula Officinalis MT, Hypericum Perforatum MT, 30X, Arsenicum Album 12X, Belladonna 12X, Cantharis 12X, Causticum 12X, Picricum Acidum 12X, Urtica Urens 12X.

INDICATIONS:

For temporary relief of minor burns.

WARNINGS:

For external use only.

If pregnant or breast-feeding, ask a health care professional before use.

Keep out of reach of children. In case of overdose, get medical help or contact a Poison Control Center right away.

Do not use if tamper evident seal is broken or missing.

Store in cool, dry place.

Do not get in your eyes. If you get Burn Aide in your eyes, rinse immediately with cool tap water. In case of serious burns, consult a doctor. If your symptoms do not get better in seven days or if they get worse, check with your doctor.

Keep out of reach of children. In case of overdose, get medical help or contact a Poison Control Center right away.

DIRECTIONS:

Clean the affected area. Spray on affected area as needed.

INDICATIONS:

For temporary relief of minor burns.

INACTIVE INGREDIENTS:

Demineralized Water, Aloe Vera Thickened Gel (Aloe Barbadensis Leaf Juice, Water, Benzyl Alcohol (and) Ethylhexylglycerin (and) Tocopherol, Acrylates/C10-30 Alkyl Acrylate Crosspolymer, Disodium EDTA Sodium Hydroxide), 10.7% Ethanol.

QUESTIONS:

Distributed by:

BioActive Nutritional, Inc.

1803 N. Wickham Rd.

Melbourne, FL 32935

bioactivenutritional.com

PACKAGE LABEL DISPLAY:

BIOActive Nutritional

BURN AIDE

HOMEOPATHIC

4 FL OZ (120 ml)